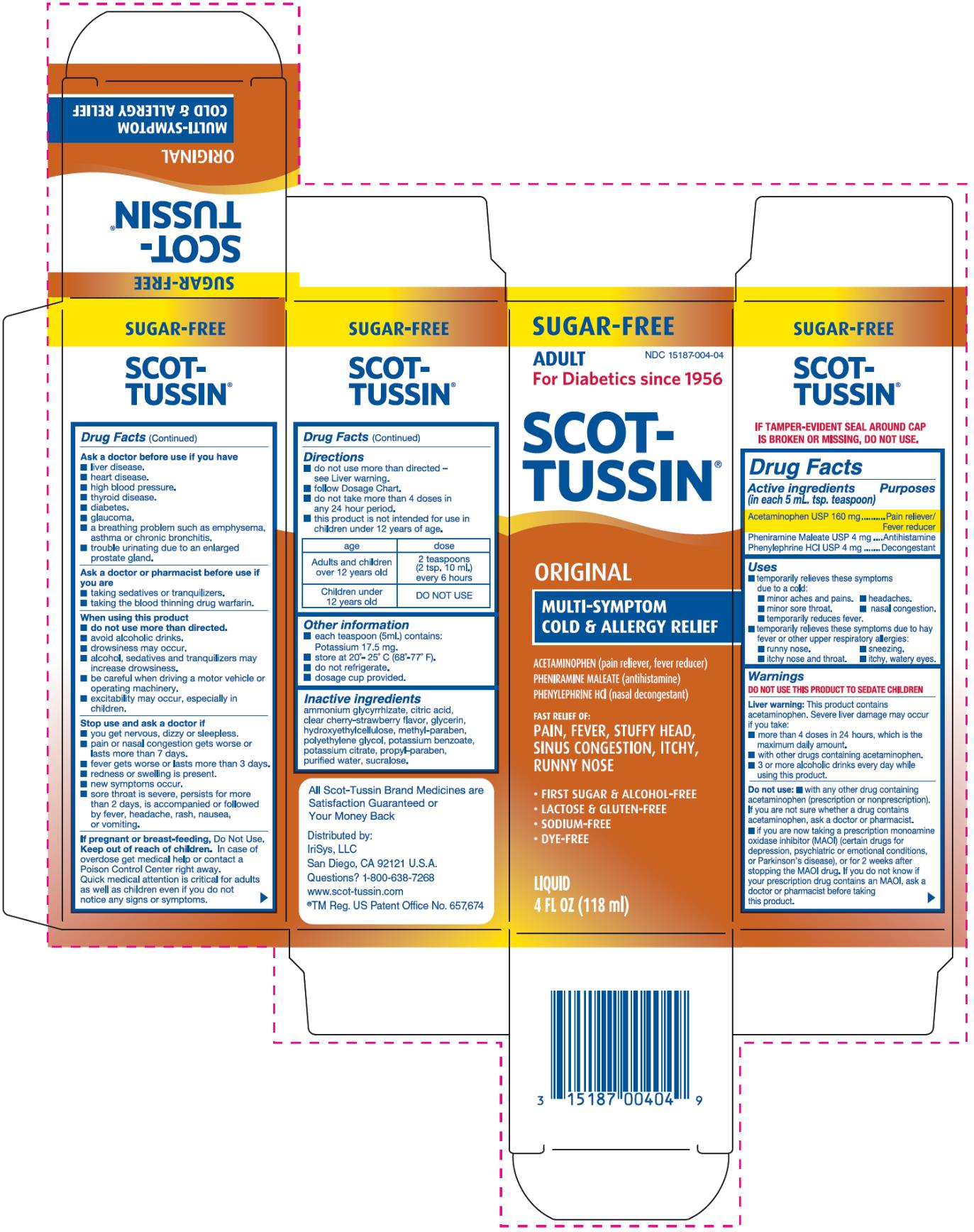 DRUG LABEL: Scot-Tussin Original Multi-Symptom Cold and Allergy Relief
NDC: 15187-004 | Form: LIQUID
Manufacturer: IriSys, LLC
Category: otc | Type: HUMAN OTC DRUG LABEL
Date: 20151015

ACTIVE INGREDIENTS: ACETAMINOPHEN 160 mg/5 mL; PHENYLEPHRINE HYDROCHLORIDE 4 mg/5 mL; PHENIRAMINE MALEATE 4 mg/5 mL
INACTIVE INGREDIENTS: AMMONIUM GLYCYRRHIZATE; CITRIC ACID MONOHYDRATE; GLYCERIN; HYDROXYETHYL CELLULOSE (2000 MPA.S AT 1%); METHYLPARABEN; POLYETHYLENE GLYCOLS; POTASSIUM BENZOATE; POTASSIUM CITRATE; PROPYLPARABEN; WATER; SUCRALOSE

Scot-Tussin Original Multi-Symptom Cold and Allergy Relief

Drug Facts

Active ingredient (in each 5 mL tsp. teaspoon)

Acetaminophen USP 160 mg

Purpose

Pain reliever/Fever reducer

Active ingredient (in each 5 mL tsp. teaspoon)

Pheniramine Maleate USP 4 mg

Purpose

Antihistamine

Active ingredient (in each 5 mL tsp. teaspoon)

Phenylephrine HCI USP 4 mg

Purpose

Decongestant

Uses

- temporarily relieves these symptoms due to a cold:
  - minor aches and pains.
  - headaches.
  - minor sore throat.
  - nasal congestion.
  - temporarily reduces fever.
- temporarily relieves these symptoms due to hay fever or other upper respiratory allergies:
  - runny nose.
  - sneezing.
  - itchy nose and throat.
  - itchy, watery eyes.

Warnings

DO NOT USE THIS PRODUCT TO SEDATE CHILDREN

Liver warning: This product contains acetaminophen. Severe liver damage may occur if you take:

- more than 4 doses in 24 hours, which is the maximum daily amount.
- with other drugs containing acetaminophen.
- 3 or more alcoholic drinks every day while using this product.

Do not use:

- with any other drug containing acetaminophen (prescription or nonprescription).
  if you are not sure whether a drug contains acetaminophen, ask a doctor or pharmacist.
- if you are now taking a prescription monoamine oxidase inhibitor (MAOI) (certain drugs for depression, psychiatric or emotional conditions, or Parkinson’s disease), or for 2 weeks after stopping the MAOI drug. If you do not know if your prescription drug contains an MAOI, ask a doctor or pharmacist before taking this product.

Ask a doctor before use if you have

- liver disease.
- heart disease.
- high blood pressure.
- thyroid disease.
- diabetes.
- glaucoma.
- a breathing problem such as emphysema, asthma or chronic bronchitis.
- trouble urinating due to an enlarged prostate gland.

Ask a doctor or pharmacist before use if you are

- taking sedatives or tranquilizers.
- taking the blood thinning drug warfarin.

When using this product

- do not use more than directed.
- avoid alcoholic drinks.
- drowsiness may occur.
- alcohol, sedatives and tranquilizers may increase drowsiness.
- be careful when driving a motor vehicle or operating machinery.
- excitability may occur, especially in children.

Stop use and ask a doctor if

- you get nervous, dizzy or sleepless.
- pain or nasal congestion gets worse or lasts more than 7 days.
- fever gets worse or lasts more than 3 days.
- redness or swelling is present.
- new symptoms occur.
- sore throat is severe, persists for more than 2 days, is accompanied or followed by fever, headache, rash, nausea, or vomiting.

If pregnant or breast-feeding,

Do Not Use.

Keep out of reach of children.

In case of overdose get medical help or contact a Poison Control Center right away. Quick medical attention is critical for adults as well as children even if you do not notice any signs or symptoms.

Directions

- do not use more than directed – see Liver warning.
- follow Dosage Chart.
- do not take more than 4 doses in any 24 hour period.
- this product is not intended for use in children under 12 years of age.

age | dose
Adults and children over 12 years old | 2 teaspoons (2 tsp. 10 mL) every 6 hours
Children under 12 years old | DO NOT USE

Other information

- each teaspoon (5 mL) contains: Potassium 17.5 mg.
- store at 20°- 25° C (68°-77°F).
- do not refrigerate.
- dosage cup provided

Inactive ingredients

ammonium glycyrrhizate, citric acid, clear cherry-strawberry flavor, glycerin, hydroxyethylcelluose, methyl-paraben, polyethylene glycol, potassium benzoate, potassium citrate, propyl-paraben, purified water, sucralose.

Distributed by:
IriSys, LLC
San Diego, CA 92121 U.S.A.
Questions? 1-800-638-7268
www.scot-tussin.com
®TM Reg. US Patent Office No. 657, 674

PRINCIPAL DISPLAY PANEL

SUGAR-FREE
ADULT
NDC 15187-004-04
For Diabetics since 1956
SCOT-TUSSIN®
ORIGINAL
MULTI-SYMPTOM
COLD & ALLERGY RELIEF
ACETAMINOPHEN (pain reliever, fever reducer)
PHENIRAMINE MALEATE (antihistamine)
PHENYLEPHRINE HCI (nasal decongestant)

FAST RELIEF OF:
PAIN, FEVER, STUFFY HEAD,
SINUS CONGESTION, ITCHY,
RUNNY NOSE

- FIRST SUGAR & ALCOHOL-FREE
- LACTOSE & GLUTEN-FREE
- SODIUM-FREE
- DYE-FREE

LIQUID
4 FL OZ (118 ml)